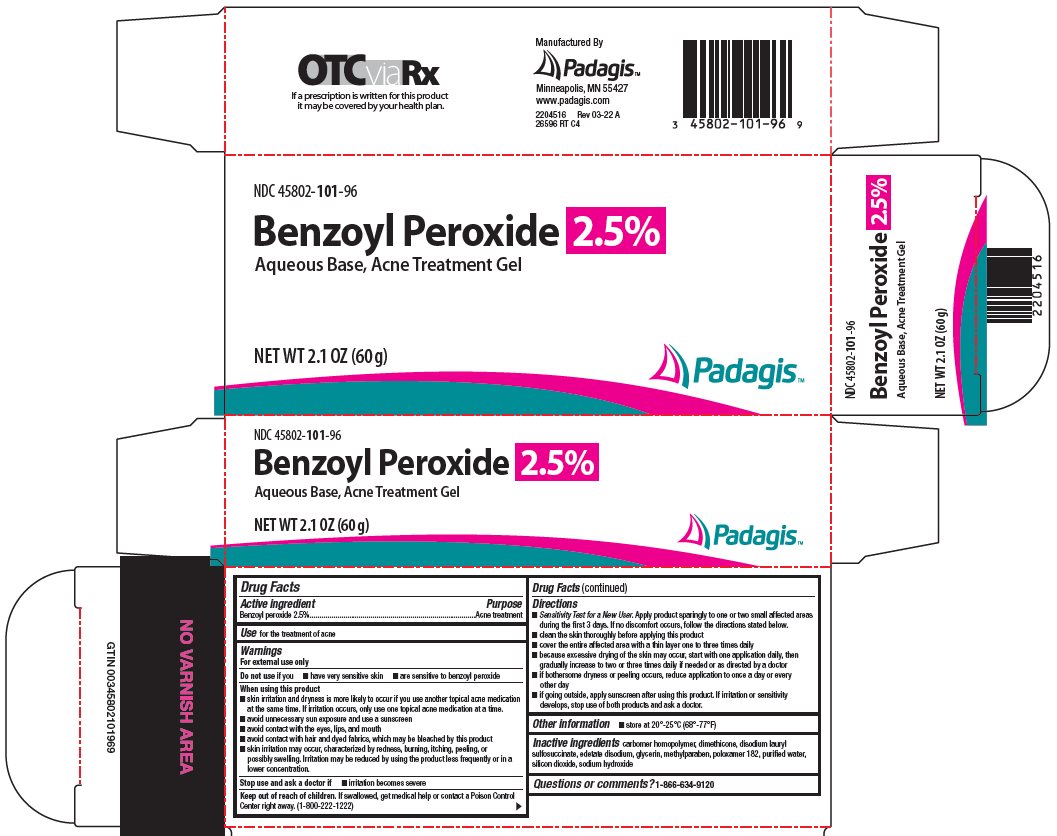 DRUG LABEL: benzoyl peroxide
NDC: 45802-101 | Form: GEL
Manufacturer: Padagis Israel Pharmaceuticals Ltd
Category: otc | Type: HUMAN OTC DRUG LABEL
Date: 20241023

ACTIVE INGREDIENTS: BENZOYL PEROXIDE 2.5 g/100 g
INACTIVE INGREDIENTS: DIMETHICONE, UNSPECIFIED; DISODIUM LAURYL SULFOSUCCINATE; EDETATE DISODIUM; GLYCERIN; METHYLPARABEN; POLOXAMER 182; WATER; SILICON DIOXIDE; SODIUM HYDROXIDE

Benzoyl Peroxide 2.5% Drug Facts

Active ingredient

Benzoyl peroxide 2.5%

Purpose

Acne treatment

Use

for the treatment of acne

Warnings

For external use only

Do not use

if you

- have very sensitive skin
- are sensitive to benzoyl peroxide

When using this product

- skin irritation and dryness is more likely to occur if you use another topical acne medication at the same time. If irritation occurs, only use one topical acne medication at a time.
- avoid unnecessary sun exposure and use a sunscreen
- avoid contact with the eyes, lips, and mouth
- avoid contact with hair and dyed fabrics, which may be bleached by this product
- skin irritation may occur, characterized by redness, burning, itching, peeling, or possibly swelling. Irritation may be reduced by using the product less frequently or in a lower concentration.

Stop use and ask a doctor if

- irritation becomes severe

Keep out of reach of children.

If swallowed, get medical help or contact a Poison Control Center right away. (1-800-222-1222)

Directions

- Sensitivity Test for a New User. Apply product sparingly to one or two small affected areas during the first 3 days. If no discomfort occurs, follow the directions stated below.
- clean the skin thoroughly before applying this product
- cover the entire affected area with a thin layer one to three times daily
- because excessive drying of the skin may occur, start with one application daily, then gradually increase to two or three times daily if needed or as directed by a doctor
- if bothersome dryness or peeling occurs, reduce application to once a day or every other day
- if going outside, apply sunscreen after using this product. If irritation or sensitivity develops, stop use of both products and ask a doctor.

Other information

- store at 20°-25° (68°-77°F)

Inactive ingredients

carbomer homopolymer, dimethicone, disodium lauryl sulfosuccinate, edetate disodium, glycerin, methylparaben, poloxamer 182, purified water, silicon dioxide, sodium hydroxide

Questions or comments?

1-866-634-9120

Package/Label Principal Display Panel

NDC 45802-101-96

Benzoyl Peroxide 2.5%

Aqueous Base, Acne Treatment Gel

NET WT 2.1 OZ (60 g)